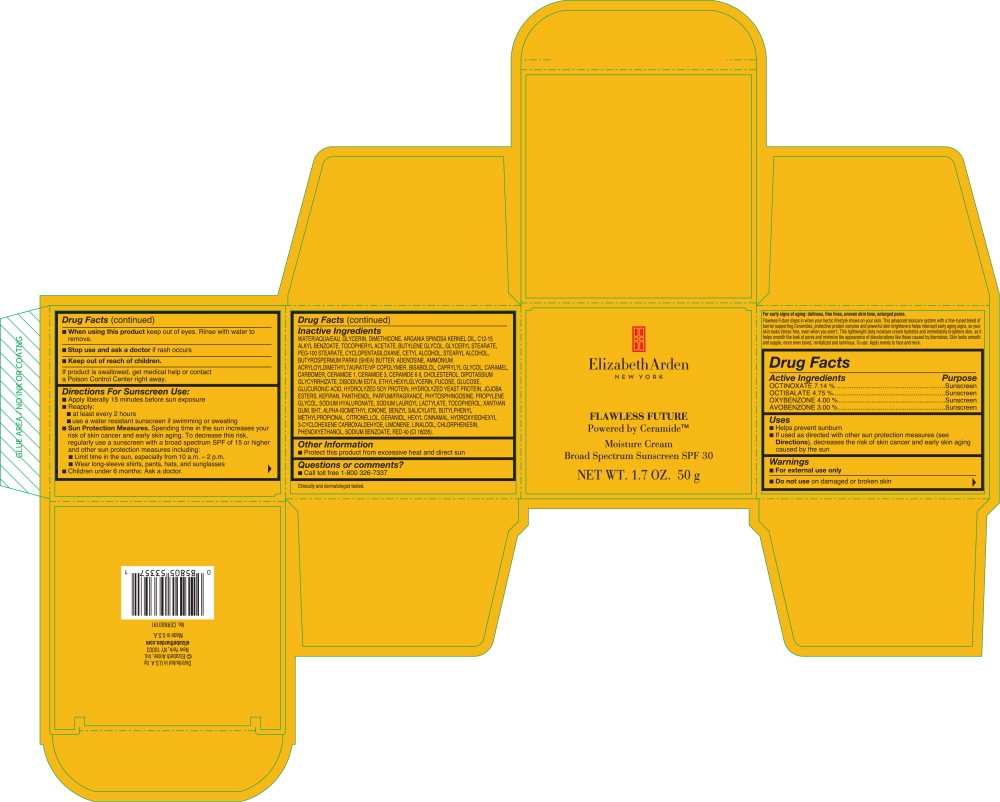 DRUG LABEL: FLAWLESS FUTURE MOISTURE
NDC: 67938-2050 | Form: CREAM
Manufacturer: ELIZABETH ARDEN, INC
Category: otc | Type: HUMAN OTC DRUG LABEL
Date: 20141107

ACTIVE INGREDIENTS: OCTINOXATE 3.57 g/1 g; OCTISALATE 2.375 g/1 g; OXYBENZONE 2 g/1 g; AVOBENZONE 1.5 g/1 g
INACTIVE INGREDIENTS: WATER; GLYCERIN; DIMETHICONE; ARGAN OIL; C12-15 ALKYL BENZOATE; .ALPHA.-TOCOPHEROL ACETATE; BUTYLENE GLYCOL; GLYCERYL MONOSTEARATE; PEG-100 STEARATE; CYCLOMETHICONE 5; CETYL ALCOHOL; STEARYL ALCOHOL; SHEA BUTTER; PHENOXYETHANOL; AMMONIUM ACRYLOYLDIMETHYLTAURATE/VP COPOLYMER; PANTHENOL; JOJOBA OIL, RANDOMIZED; XANTHAN GUM; CHLORPHENESIN; LEVOMENOL; CAPRYLYL GLYCOL; GLYCYRRHIZINATE DIPOTASSIUM; EDETATE DISODIUM; SODIUM LAUROYL LACTYLATE; ADENOSINE; LINALOOL, (+/-)-; PROPYLENE GLYCOL; BUTYLPHENYL METHYLPROPIONAL; CARAMEL; LIMONENE, (+)-; BENZYL SALICYLATE; CERAMIDE 3; HYALURONATE SODIUM; BUTYLATED HYDROXYTOLUENE; DEXTROSE; ISOMETHYL-.ALPHA.-IONONE; CERAMIDE 6 II; PHYTOSPHINGOSINE; CHOLESTEROL; HYDROXYISOHEXYL 3-CYCLOHEXENE CARBOXALDEHYDE; .ALPHA.-HEXYLCINNAMALDEHYDE; ETHYLHEXYLGLYCERIN; FUCOSE; GLUCURONIC ACID; SODIUM BENZOATE; SOY PROTEIN; GERANIOL; .BETA.-CITRONELLOL, (R)-; YEAST, UNSPECIFIED; TOCOPHEROL; SOLVENT RED 4; CERAMIDE 1

Drug Facts

Active Ingredients

OCTINOXATE 7.14 %

OCTISALATE 4.75 %

OXYBENZONE 4.00 %

AVOBENZONE 3.00 %

Purpose

Sunscreen

Sunscreen

Sunscreen

Sunscreen

Uses

- Helps prevent sunburn
- If used as directed with other sun protection measures (see Directions), decreases the risk of skin cancer and early skin aging caused by the sun

Warnings

- For external use only

- Do not use on damaged or broken skin

- When using this product keep out of eyes. Rinse with water to remove.

- Stop use and ask a doctor if rash occurs

- Keep out of reach of children.

If product is swallowed, get medical help or contact a Poison Control Center right away.

Directions For Sunscreen Use:

- Apply liberally 15 minutes before sun exposure
- Reapply:
  - at least every 2 hours
  - use a water resistant sunscreen if swimming or sweating
- Sun Protection Measures. Spending time in the sun increases your risk of skin cancer and early skin aging. To decrease this risk, regularly use a sunscreen with a broad spectrum SPF of 15 or higher and other sun protection measures including:
  - Limit time in the sun, especially from 10 a.m. - 2 p.m.
  - Wear long-sleeve shirts, pants, hats, and sunglasses
- Children under 6 months: Ask a doctor.

Inactive Ingredients

WATER/AQUA/EAU, GLYCERIN, DIMETHICONE, ARGANIA SPINOSA KERNEL OIL, C12-15 ALKYL BENZOATE, TOCOPHERYL ACETATE, BUTYLENE GLYCOL, GLYCERYL STEARATE, PEG-100 STEARATE, CYCLOPENTASILOXANE, CETYL ALCOHOL, STEARYL ALCOHOL, BUTYROSPERMUM PARKII (SHEA) BUTTER, ADENOSINE, AMMONIUM ACRYLOYLDIMETHYLTAURATE/VP COPOLYMER, BISABOLOU CAPRYLYL GLYCOL, CARAMEL, CARBOMER, CERAMIDE1, CERAMIDE3, CERAMIDE6 II, CHOLESTEROL, DIPOTASSIUM GLYCYRRHIZATE, DISODIUM EDTA, ETHYLHEXYLGLYCERIN, FUCOSE, GLUCOSE, GLUCURONIC ACID, HYDROLYZED SOY PROTEIN, HYDROLYZED YEAST PROTEIN, JOJOBA ESTERS, KEFIRAN, PANTHENOL, PARFUM/FRAGRANCE, PHYTOSPHINGOSINE, PROPYLENE GLYCOL, SODIUM HYALURONATE, SODIUM LAUROYL LACTYLATE, TOCOPHEROL, XANTHAN GUM, BHT, ALPHA-ISOMETHYLIONONE, BENZYL SALICYLATE, BUTYLPHENYL METHYLPROPIONAL, CITRONELLOL, GERANIOL, HEXYL CINNAMAL, HYDROXYISOHEXYL 3-CYCLOHEXENE CARBOXALDEHYDE, LIMONENE, LINALOOL, CHLORPHENESIN, PHENOXYETHANOL, SODIUM BENZOATE, RED 40 (Cl 16035).

Other Information

- Protect this product from excessive heat and direct sun

Questions or comments?

- Call toll free 1-800 326-7337

Principal Display Panel - Box Label

Elizabeth Arden
NEW YORK

FLAWLESS FUTURE

Powered by Ceramide™

Moisture Cream
Broad Spectrum Sunscreen SPF 30

NET WT. 1.7 OZ. 50 g